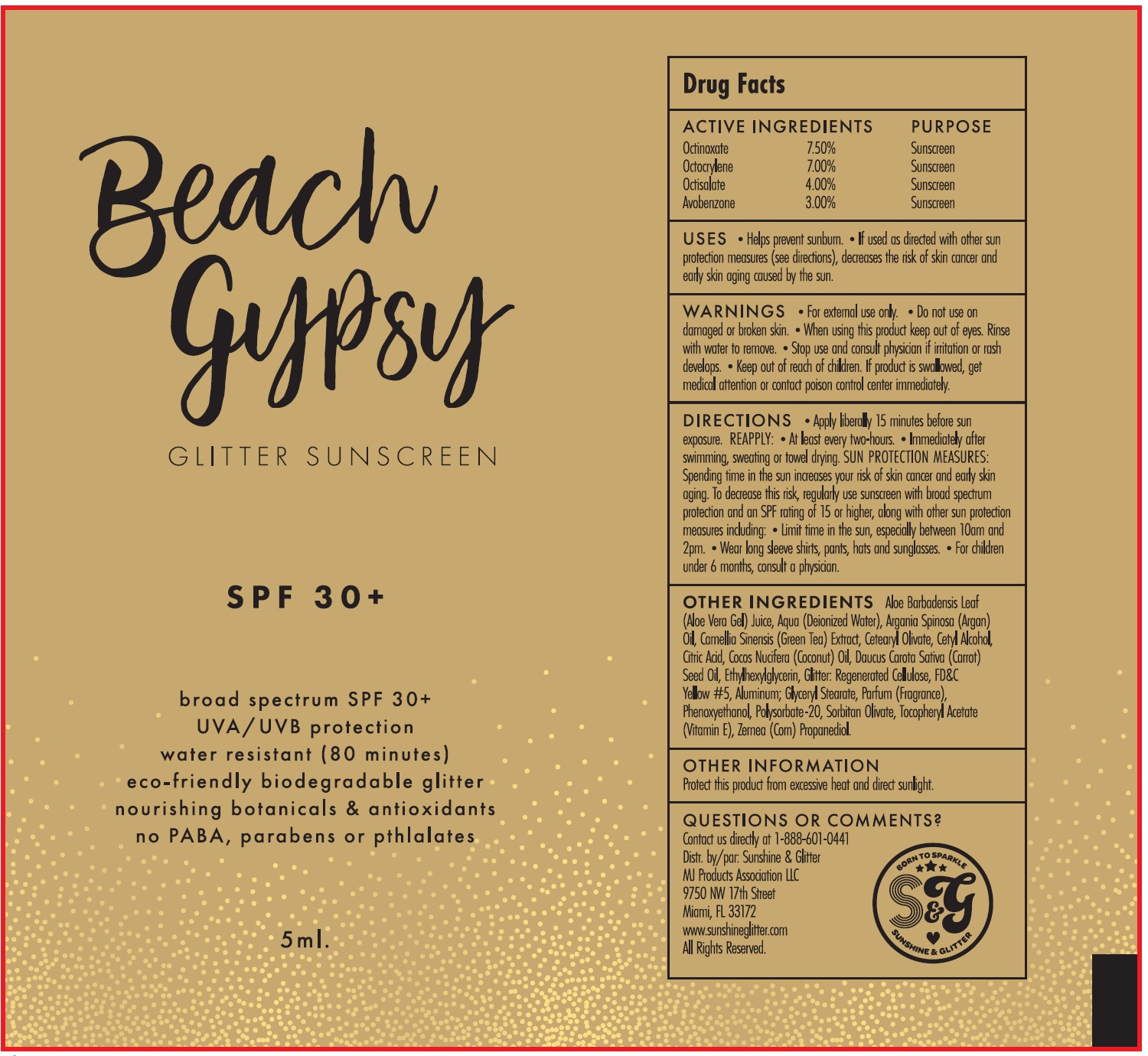 DRUG LABEL: BEACH GYPSY Glitter Sunscreen SPF 30
NDC: 72085-312 | Form: CREAM
Manufacturer: MJ Products Association, LLC
Category: otc | Type: HUMAN OTC DRUG LABEL
Date: 20231105

ACTIVE INGREDIENTS: OCTINOXATE 75 mg/1 mL; OCTOCRYLENE 70 mg/1 mL; OCTISALATE 40 mg/1 mL; AVOBENZONE 30 mg/1 mL
INACTIVE INGREDIENTS: ALOE VERA LEAF; WATER; ARGAN OIL; GREEN TEA LEAF; CETEARYL OLIVATE; CETYL ALCOHOL; CITRIC ACID MONOHYDRATE; COCONUT OIL; CARROT SEED OIL; ETHYLHEXYLGLYCERIN; REGENERATED CELLULOSE; FD&C YELLOW NO. 5; ALUMINUM; GLYCERYL MONOSTEARATE; PHENOXYETHANOL; POLYSORBATE 20; SORBITAN OLIVATE; .ALPHA.-TOCOPHEROL ACETATE; CORN; PROPANEDIOL

BEACH GYPSY Glitter Sunscreen SPF-30

ACTIVE INGREDIENTS

Homosalate 10.00%

Octocrylene 5.00%

Octisalate 5.00%

Zinc Oxide 4.00%

PURPOSE

Sunscreen

USES

- Helps prevent sunburn.
- If used as directed with other sun protection measures (see directions), decreases the risk of skin cancer and early skin aging caused by the sun.

WARNINGS

For external use only.

Do not use

- on damaged or broken skin.

When using this product

keep out of eyes. Rinse with water to remove.

Stop use and consult physician

if irritation or rash develops.

Keep out of reach of children.

If product is swallowed, get medical attention or contact poison control center immediately.

Directions

- Apply liberally 15 minutes before sun exposure.

- At least every two-hours.
- Immediately after swimming, sweating or towel drying. SUN PROTECTION MEASURES: Spending time in the sun increases your risk of skin cancer and early skin aging. To decrease this risk, regularly use suncreen with broad spectrum protection and on SPF rating of 15 or higher, along with other sun protection measures including: Limit time in the sun, especially between 10am and 2pm.
- Wear long sleeve shirts, pants, hats, and sunglasses.
- For children under 6 months, consult a physician.

REAPPLY:

Other Ingredients

Aloe Barbadensis Leaf (Aloe Vera Gel), Juice, Aqua (Deionized Water), Argania Spinosa (Argan) Oil, Camellia Sinensis (Green Tea) Extract, Cetearyl Olivate, Cetyl Alcohol, Citric Acid, Cocos Nucifera (Coconut) Oil, Daucus Carota Sativa (Carrot) Seed Oil, Ethylhexylglycerin, Glitter: Regenerated Cellulose/Rayon, FD&C Yellow #5, Aluminum; Glyceryl Stearate, Parfum (Fragrance), Phenoxyethanol, Polysorbate-20, Sorbitan Olivate, Tocopherol Acetate (Vitamin E), Zemea (Corn) Propanediol.

Other Information

Protect this product from excessive heat and direct sunlight.

Questions or comments?

Contact us directly at 1-888-601-0441